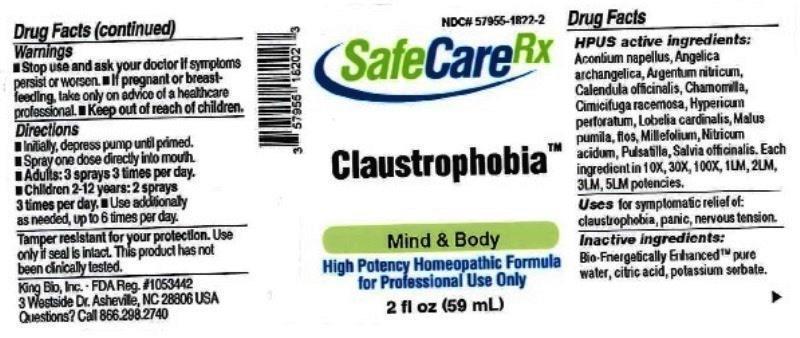 DRUG LABEL: Claustrophobia
NDC: 57955-1822 | Form: LIQUID
Manufacturer: King Bio Inc.
Category: homeopathic | Type: HUMAN OTC DRUG LABEL
Date: 20161202

ACTIVE INGREDIENTS: ACONITUM NAPELLUS 10 [hp_X]/59 mL; ANGELICA ARCHANGELICA ROOT 10 [hp_X]/59 mL; SILVER NITRATE 10 [hp_X]/59 mL; CALENDULA OFFICINALIS FLOWERING TOP 10 [hp_X]/59 mL; MATRICARIA RECUTITA 10 [hp_X]/59 mL; BLACK COHOSH 10 [hp_X]/59 mL; HYPERICUM PERFORATUM 10 [hp_X]/59 mL; LOBELIA CARDINALIS 10 [hp_X]/59 mL; MALUS DOMESTICA FLOWER 10 [hp_X]/59 mL; ACHILLEA MILLEFOLIUM 10 [hp_X]/59 mL; NITRIC ACID 10 [hp_X]/59 mL; PULSATILLA VULGARIS 10 [hp_X]/59 mL; SAGE 10 [hp_X]/59 mL
INACTIVE INGREDIENTS: WATER; ANHYDROUS CITRIC ACID; POTASSIUM SORBATE

Claustrophobia™

ACTIVE INGREDIENT

Drug Facts__________________________________________________________________________________________________________

HPUS active ingredients: Aconitum napellus, Angelica archangelica, Argentum nitricum, Calendula officinalis, Chamomilla, Cimicifuga racemosa, Lobelia cardinalis, Malus pumila, flos, Millefolim, Nitricum acidum, Pulsatilla, Salvia officinalis. Equal volumes of each ingredient in 10X, 30X, 100X, 1LM, 2LM, 3LM, 5LM potencies.

INDICATIONS AND USAGE

Uses for symptomatic relief of: claustrophobia, panic, nervous tension.

Inactive Ingredients:

Bio-Energetically Enhanced™ pure water, citric acid and potassium sorbate.

Warnings

- Stop use and ask your doctor if symptoms persist or worsen.
- If pregnant or breast-feeding, take only on advice of a healthcare professional.

- Keep out of reach of children.

Directions

- Initially, depress pump until primed.
- Spray one dose directly into mouth.
- Adults: 3 sprays 3 times per day.
- Children (2-12 years): 2 sprays 3 times per day.
- Use additionally as needed, up to 6 times per day.

OTHER SAFETY INFORMATION

Tamper resistant for your protection. Use only if safety seal is intact. This product has not been clinically tested.

PURPOSE

Uses for symptomatic relief of:

- claustrophobia
- panic
- nervous tension